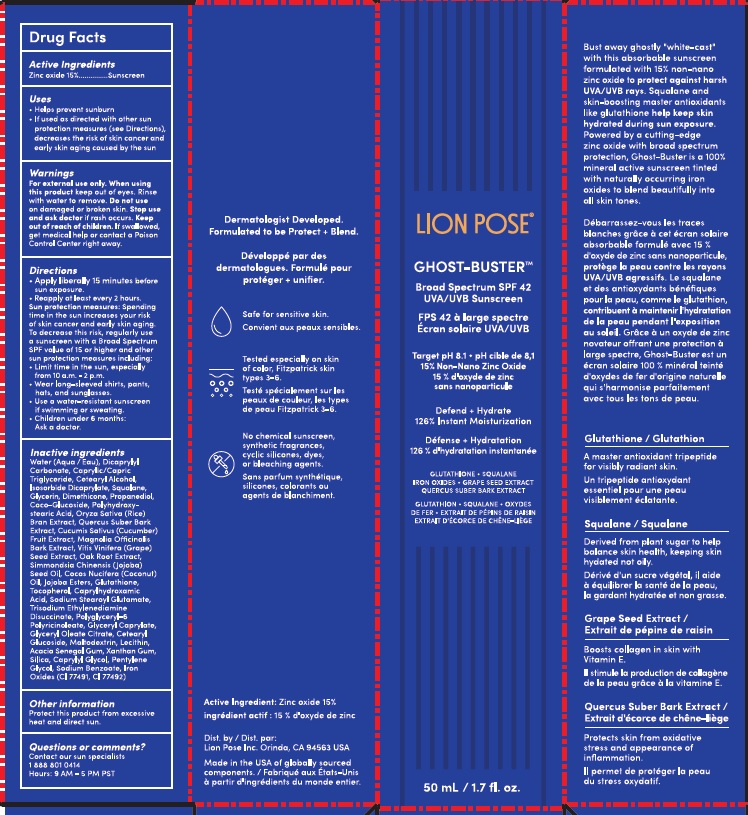 DRUG LABEL: LION POSE GHOST-BUSTER BROAD SPECTRUM SPF 42 SUNSCREEN
NDC: 83605-001 | Form: LOTION
Manufacturer: Lion Pose Inc.
Category: otc | Type: HUMAN OTC DRUG LABEL
Date: 20251017

ACTIVE INGREDIENTS: ZINC OXIDE 150 mg/1 mL
INACTIVE INGREDIENTS: CAPRYLHYDROXAMIC ACID; WATER; MEDIUM-CHAIN TRIGLYCERIDES; JOJOBA OIL, RANDOMIZED; CETOSTEARYL ALCOHOL; GLUTATHIONE; MALTODEXTRIN; PENTYLENE GLYCOL; QUERCUS SUBER BARK; CUCUMBER; VITIS VINIFERA SEED; FERRIC OXIDE RED; GLYCERIN; MAGNOLIA OFFICINALIS BARK; ISOSORBIDE DICAPRYLATE; SQUALANE; JOJOBA OIL; GLYCERYL CAPRYLATE; POLYHYDROXYSTEARIC ACID (2300 MW); COCONUT OIL; TOCOPHEROL; ACACIA; XANTHAN GUM; DICAPRYLYL CARBONATE; PROPANEDIOL; CETEARYL GLUCOSIDE; SODIUM BENZOATE; SODIUM STEAROYL GLUTAMATE; CAPRYLYL GLYCOL; TRISODIUM ETHYLENEDIAMINE DISUCCINATE; GLYCERYL MONOOLEATE CITRATE; DIMETHICONE; COCO GLUCOSIDE; LECITHIN, SOYBEAN; RICE BRAN; POLYGLYCERYL-6 POLYRICINOLEATE; SILICON DIOXIDE; FERRIC OXIDE YELLOW

LION POSE GHOST-BUSTER BROAD SPECTRUM SPF 42 SUNSCREEN

Active Ingredients

Zinc oxide 15%

Purpose

Sunscreen

Uses

- Helps prevent sunburn
- If used as directed with other sun protection measures (see Directions), decreases the risk of skin cancer and early skin aging caused by the sun

Warnings

For external use only.

When using this product

keep out of eyes. Rinse with water to remove.

Do not use

on damaged or broken skin.

Stop use and ask doctor

if rash occurs.

Keep out of reach of children.

If swallowed, get medical help or contact a Poison Control Center right away.

Directions

- Apply liberally 15 minutes before sun exposure.
- Reapply at least every 2 hours.
- Sun protection measures: Spending time in the sun increases your risk of skin cancer and early skin aging. To decrease this risk, regularly use a sunscreen with a Broad Spectrum SPF value of 15 or higher and other sun protection measures including:
- Limit time in the sun, especially from 10 a.m. - 2 p.m.
- Wear long-sleeved shirts, pants, hats, and sunglasses.
- Use a water-resistant sunscreen if swimming or sweating.
- Children under 6 months: Ask a doctor.

Inactive ingredients

Water (Aqua/Eau), Dicaprylyl Carbonate, Caprylic/Capric Triglyceride, Cetearyl Alcohol, Isosorbide Dicaprylate, Squalane, Glycerin, Dimethicone, Propanediol, Coco-Glucoside, Polyhydroxystearic Acid, Oryza Sativa (Rice) Bran Extract, Quercus Suber Bark Extract, Cucumis Sativus (Cucumber) Fruit Extract, Magnolia Officinalis Bark Extract, Vitis Vinifera (Grape) Seed Extract, Oak Root Extract, Simmondsia Chinensis (Jojoba) Seed Oil, Cocos Nucifera (Coconut) Oil, Jojoba Esters, Glutathione, Tocopherol, Caprylhydroxamic Acid, Sodium Stearoyl Glutamate, Trisodium Ethylenediamine Disuccinate, Polyglyceryl-6 Polyricinoleate, Glyceryl Caprylate, Glyceryl Oleate Citrate, Cetearyl Glucoside, Maltodextrin, Lecithin, Acacia Senegal Gum, Xanthan Gum, Silica, Caprylyl Glycol, Pentylene Glycol, Sodium Benzoate, Iron Oxides (CI 77491, CI 77492).

Other information

Protect this product from excessive heat and direct sun.

Questions or comments?

Contact our sun specialists

1 888 801 0414

Hours: 9 AM - 5 PM PST